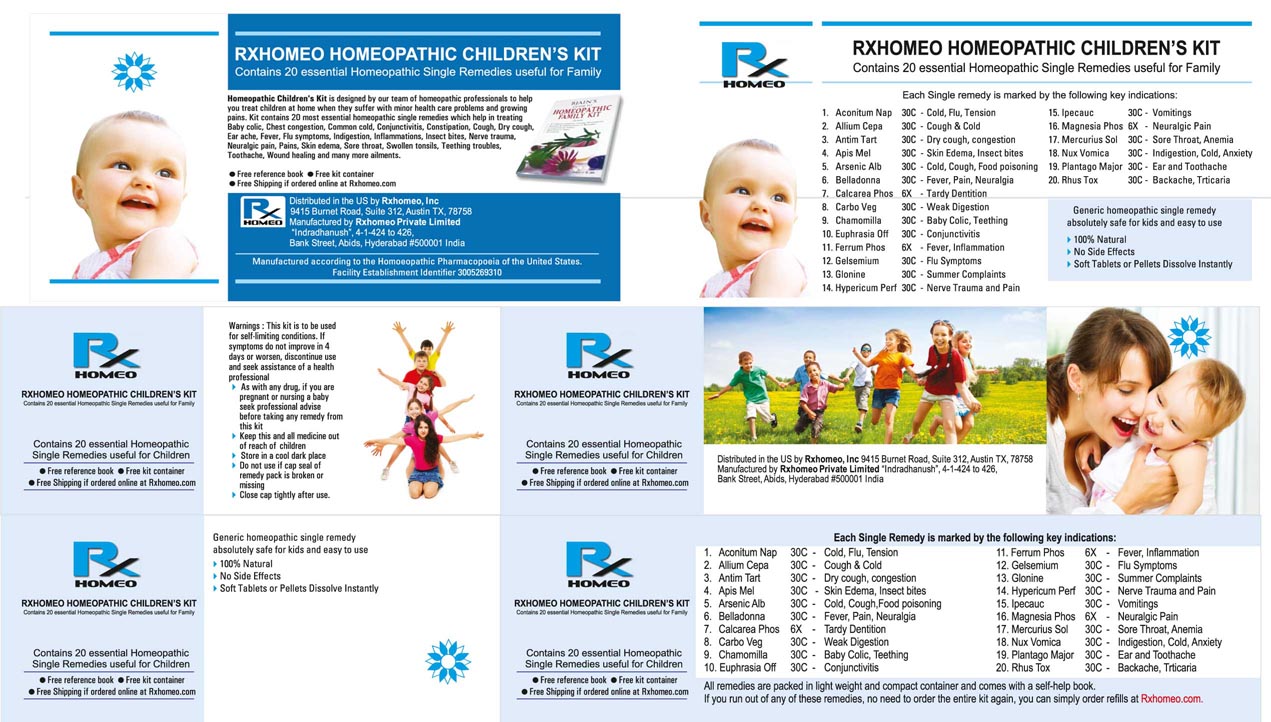 DRUG LABEL: Rxhomeo Homeopathic Childrens Kit
NDC: 15631-2452 | Form: KIT | Route: ORAL
Manufacturer: Rxhomeo Private Limited d.b.a.
Category: homeopathic | Type: HUMAN OTC DRUG LABEL
Date: 20160729

ACTIVE INGREDIENTS: ACONITUM NAPELLUS 3 [hp_X]/1 1; ONION 1 [hp_X]/1 1; ANTIMONY POTASSIUM TARTRATE 3 [hp_X]/1 1; APIS MELLIFERA 1 [hp_X]/1 1; ARSENIC TRIOXIDE 6 [hp_X]/1 1; ARNICA MONTANA 3 [hp_X]/1 1; ATROPA BELLADONNA 3 [hp_X]/1 1; BRYONIA ALBA ROOT 3 [hp_X]/1 1; MATRICARIA RECUTITA 1 [hp_X]/1 1; EUPHRASIA STRICTA 1 [hp_X]/1 1; GELSEMIUM SEMPERVIRENS ROOT 3 [hp_X]/1 1; NITROGLYCERIN 6 [hp_X]/1 1; HYPERICUM PERFORATUM 3 [hp_X]/1 1; IPECAC 3 [hp_X]/1 1; MERCURIUS SOLUBILIS 6 [hp_X]/1 1; STRYCHNOS NUX-VOMICA SEED 3 [hp_X]/1 1; PODOPHYLLUM 3 [hp_X]/1 1; TOXICODENDRON PUBESCENS LEAF 3 [hp_X]/1 1; FERROSOFERRIC PHOSPHATE 1 [hp_X]/1 1; CALENDULA OFFICINALIS FLOWERING TOP 1 [hp_X]/1 g
INACTIVE INGREDIENTS: SUCROSE; SUCROSE; SUCROSE; SUCROSE; SUCROSE; SUCROSE; SUCROSE; SUCROSE; SUCROSE; SUCROSE; SUCROSE; SUCROSE; SUCROSE; SUCROSE; SUCROSE; SUCROSE; SUCROSE; SUCROSE; LACTOSE; ALOE

ACTIVE INGREDIENT

ACONITUM NAPELLUS

ALLIUM CEPA

ANTIMONIUM TARTARICUM

APIS MELLIFICA

ARNICA MONTANA

ARSENICUM ALBUM

BELLADONNA

BRYONIA ALBA

CHAMOMILLA

EUPHRASIA OFFICINALIS

GELSEMIUM SEMPERVIRENS

GLONOINUM

HYPERICUM PERFORATUM

IPECACUANHA

MERCURIUS SOLUBILIS

NUX VOMICA

PODOPHYLLUM PELTATUM

RHUS TOXICODENDRON

FERRUM PHOSPHORICUM

CALENDULA OFFICINALIS

USES

ACONITUM NAPELLUS | 3X | Cold, Flu, Tension
ALLIUM CEPA | 1X | Cough & Cold
ANTIMONIUM TARTARICUM | 3X | Dry Cough, Congestion
APIS MELLIFICA | 1X | Skin Edema, Insect Bites
ARNICA MONTANA | 3X | Bruises, Aches, Pains
ARSENICUM ALBUM | 6X | Weakness, Exhaustion
BELLADONNA | 3X | Fever, Pain, Neuralgia
BRYONIA ALBA | 3X | Flu, Rheumatism
CHAMOMILLA | 1X | Baby Colic, Teething
EUPHRASIA OFFICINALIS | 1X | Conjunctivitis
GELSEMIUM SEMPERVIRENS | 3X | Flu Symptoms
GLONOINUM | 6X | Congestive Headache
HEPAR SULPHURIS CALCAREUM | 1X | Croupy Cough, Boils
HYPERICUM PERFORATUM | 3X | Nerve Trauma & Pain
IPECACUANHA | 3X | Nausea, Vomiting, Cough
MERCURIUS SOLUBILIS | 6X | Sore Throat, Anemia
NUX VOMICA | 3X | Indigestion, Cold, Anxiety
PODOPHYLLUM PELTATUM | 3X | Biliousness
RHUS TOXICODENDRON | 3X | Backache, Urticaria
FERRUM PHOSPHORICUM | 1X | Fever, Inflammation
CALENDULA OFF GEL | TINC | Minor cuts, scrapes, burns, skin irritation and diaper rash

INDICATIONS

Condition listed above or as directed by the physician

DOSAGE

PELLETS included in the Kit
Adults- Take 4 or 6 Pellets by mouth, three times daily or as suggested by physician. Children 2 years and older- take 1/2 the adult dose.

TABLETS included in the Kit
Adults- Take 4 or 6 Tablets by mouth, three times daily or as suggested by physician. Children 2 years and older- take 1/2 the adult dose.

GEL OINTMENT included in the Kit
Apply a thin layer of Gel to the affected area, repeat 3 times a day or as needed.

WARNINGS

This product is to be used for self-limiting conditions

STOP USE

If symptoms do not improve in 4 days, or worsen, discontinue use and seek assistance of health professional

KEEP OUT OF REACH OF CHILDREN

Keep this and all medication out of reach of children

Do not use if capseal is broken or missing.
Close the cap tightly after use.

INACTIVE INGREDIENTS

Sucrose for Pellets.

Aloe Vera Gel for Ointment

STORAGE

Store in a cool dark place

QUESTIONS OR COMMENTS

www.Rxhomeo.com | 1.888.2796642 | info@rxhomeo.com
Rxhomeo, Inc 9415 Burnet Road, Suite 312, Austin, TX 78758